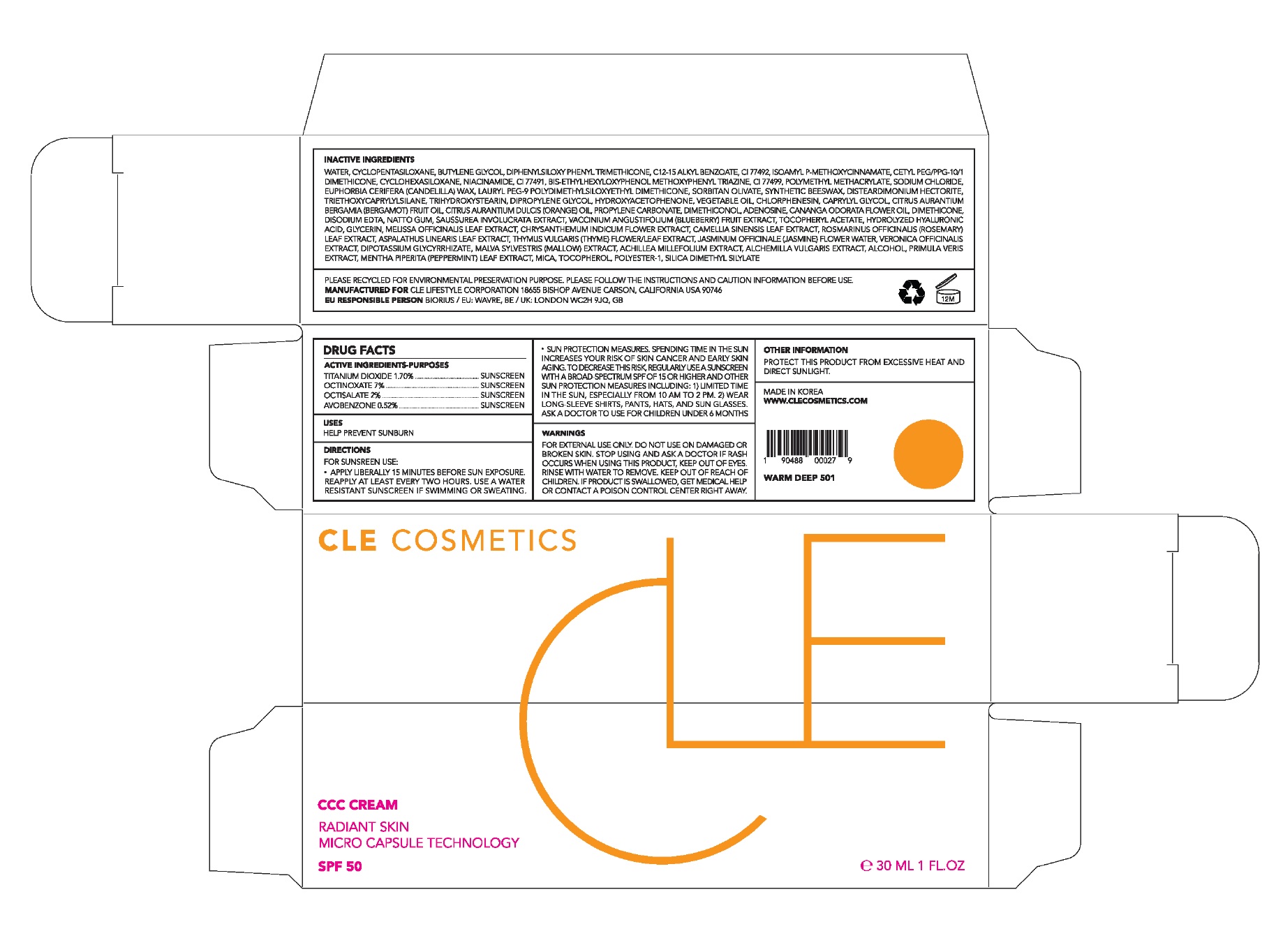 DRUG LABEL: CLE CCC Warm Deep
NDC: 69231-032 | Form: CREAM
Manufacturer: KW ABSC, INC.
Category: otc | Type: HUMAN OTC DRUG LABEL
Date: 20241219

ACTIVE INGREDIENTS: OCTINOXATE 2.1 mg/30 mL; OCTISALATE 0.6 mg/30 mL; TITANIUM DIOXIDE 0.51 mg/30 mL; AVOBENZONE 0.156 mg/30 mL
INACTIVE INGREDIENTS: CYCLOMETHICONE 5; WATER; ALKYL (C12-15) BENZOATE; CYCLOMETHICONE 6; FERRIC OXIDE YELLOW; BUTYLENE GLYCOL; AMILOXATE; CETYL PEG/PPG-10/1 DIMETHICONE (HLB 2); NIACINAMIDE; DIPHENYLSILOXY PHENYL TRIMETHICONE; MICA; BEMOTRIZINOL; POLY(METHYL METHACRYLATE; 450000 MW); FERRIC OXIDE RED; CANDELILLA WAX; SODIUM CHLORIDE; FERROSOFERRIC OXIDE; POLYESTER-10; SILICA DIMETHYL SILYLATE; DISTEARDIMONIUM HECTORITE; TRIETHOXYCAPRYLYLSILANE; SYNTHETIC BEESWAX; LAURYL PEG-9 POLYDIMETHYLSILOXYETHYL DIMETHICONE; SORBITAN OLIVATE; HYDROXYACETOPHENONE; CORN OIL; CHLORPHENESIN; DIPROPYLENE GLYCOL; CAPRYLYL GLYCOL; BERGAMOT OIL; ORANGE OIL; PROPYLENE CARBONATE; DIMETHICONOL (2000 CST); YLANG-YLANG OIL; DIMETHICONE; LOWBUSH BLUEBERRY; .ALPHA.-TOCOPHEROL ACETATE; GLYCERIN; ADENOSINE; EDETATE DISODIUM ANHYDROUS; MELISSA OFFICINALIS LEAF; CHRYSANTHEMUM INDICUM FLOWER; GREEN TEA LEAF; ROSEMARY; ASPALATHUS LINEARIS LEAF; THYME; JASMINUM OFFICINALE FLOWER; GLYCYRRHIZINATE DIPOTASSIUM; MALVA SYLVESTRIS FLOWERING TOP; ACHILLEA MILLEFOLIUM WHOLE; ALCHEMILLA XANTHOCHLORA FLOWERING TOP; ALCOHOL; PRIMULA VERIS WHOLE; MENTHA PIPERITA LEAF; TOCOPHEROL

69231-032_CLE CCC Warm Deep

ACTIVE INGREDIENT

Titanium Dioxide 1.70%

Ethylhexyl Methoxycinnamate 7.00%

Ethylhexyl Salicylate 2.00%

Avobenzone 0.52%

PURPOSE

Sunscreen

INDICATIONS AND USAGE

Helps prevent sunburn

DOSAGE AND ADMINISTRATION

Apply liberally 15 minutes before sun exposure. Reapply at least every two hours

Sun protection measures. Spending time in the sun increases your risk of skin cancer and early skin aging. To decrease this risk, regularly use a sunscreen with a broad spectrum SPF of 15 of higher and other sun protection measures including: 1) Limited time in the sun, especially from 10 am to 2 pm. 2) Wear long-sleeve shirts, pants, hats, and sunglasses
Ask a doctor to use for children under 6 months

WARNINGS

For external use only.
Do not use on damaged or broken skin.
When using this product, keep out of eyes. Rinse with water to remove.
Stop using and ask a doctor if rash occurs.

KEEP OUT OF REACH OF CHILDREN

Keep out of reach of the children. If product is swallowed, get medical help or contact a poison control center right away.

INACTIVE INGREDIENT

Water, Cyclopentasiloxane, Butylene Glycol, Diphenylsiloxy Phenyl Trimethicone, C12-15 Alkyl Benzoate, CI 77492, Isoamyl p-Methoxycinnamate, Cetyl PEG/PPG-10/1 Dimethicone, Cyclohexasiloxane, Niacinamide, CI 77491, Bis-Ethylhexyloxyphenol Methoxyphenyl Triazine, CI 77499, Polymethyl Methacrylate, Sodium Chloride, Euphorbia Cerifera (Candelilla) Wax, Lauryl PEG-9 Polydimethylsiloxyethyl Dimethicone, Sorbitan Olivate, Synthetic Beeswax, Disteardimonium Hectorite, Triethoxycaprylylsilane, Trihydroxystearin, Dipropylene Glycol, Hydroxyacetophenone, Vegetable Oil, Chlorphenesin, Caprylyl Glycol, Citrus Aurantium Bergamia (Bergamot) Fruit Oil, Citrus Aurantium Dulcis (Orange) Oil, Propylene Carbonate, Dimethiconol, Adenosine, Cananga Odorata Flower Oil, Dimethicone, Disodium EDTA, Natto Gum, Saussurea Involucrata Extract, Vaccinium Angustifolium (Blueberry) Fruit Extract, Tocopheryl Acetate, Hydrolyzed Hyaluronic Acid, Glycerin, Melissa Officinalis Leaf Extract, Chrysanthemum Indicum Flower Extract, Camellia Sinensis Leaf Extract, Rosmarinus Officinalis (Rosemary) Leaf Extract, Aspalathus Linearis Leaf Extract, Thymus Vulgaris (Thyme) Flower/Leaf Extract, Jasminum Officinale (Jasmine) Flower Water, Veronica Officinalis Extract, Dipotassium Glycyrrhizate, Malva Sylvestris (Mallow) Extract, Achillea Millefolium Extract, Alchemilla Vulgaris Extract, Alcohol, Primula Veris Extract, Mentha Piperita (Peppermint) Leaf Extract, Mica, Tocopherol, Polyester-1, Silica Dimethyl Silylate